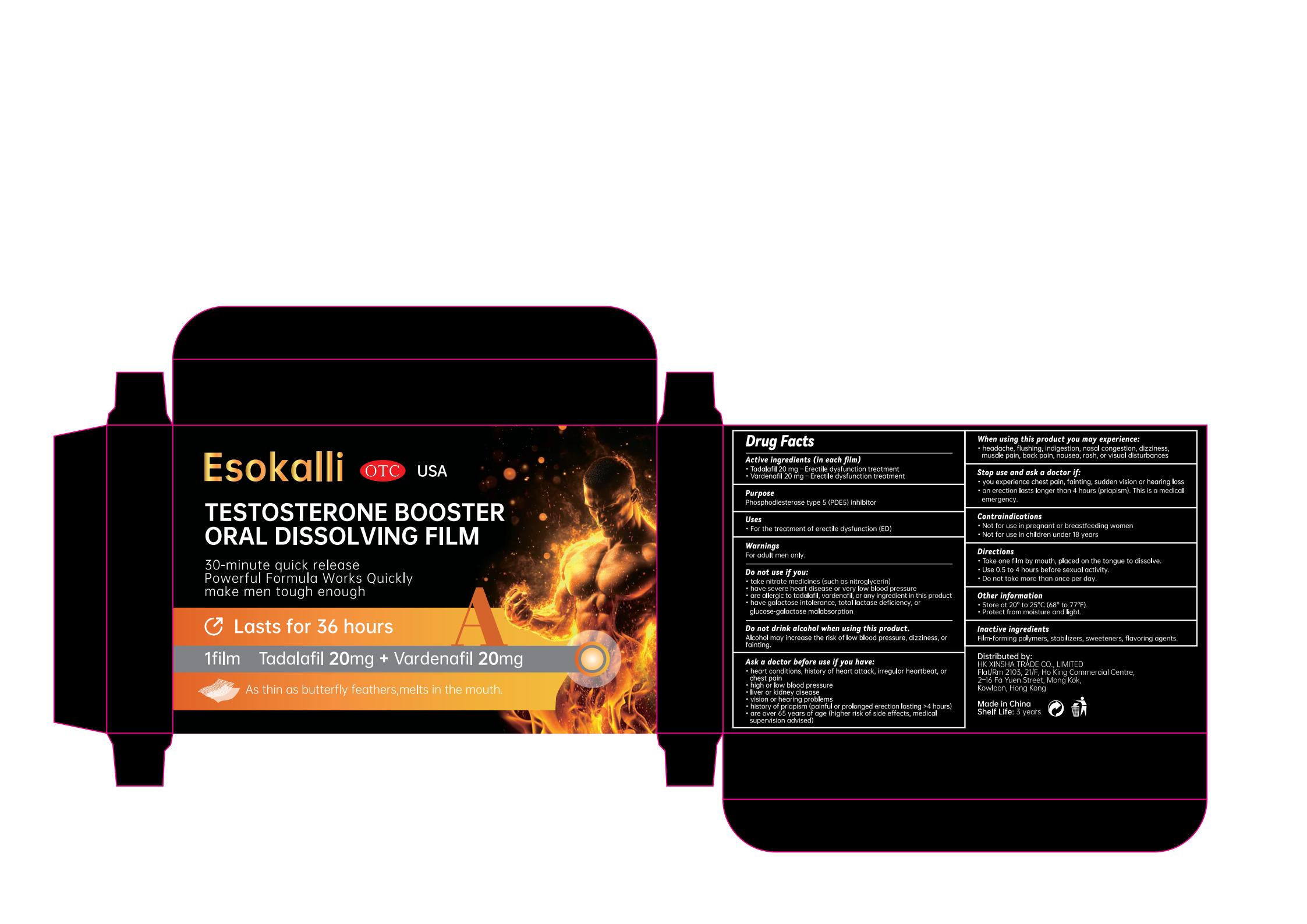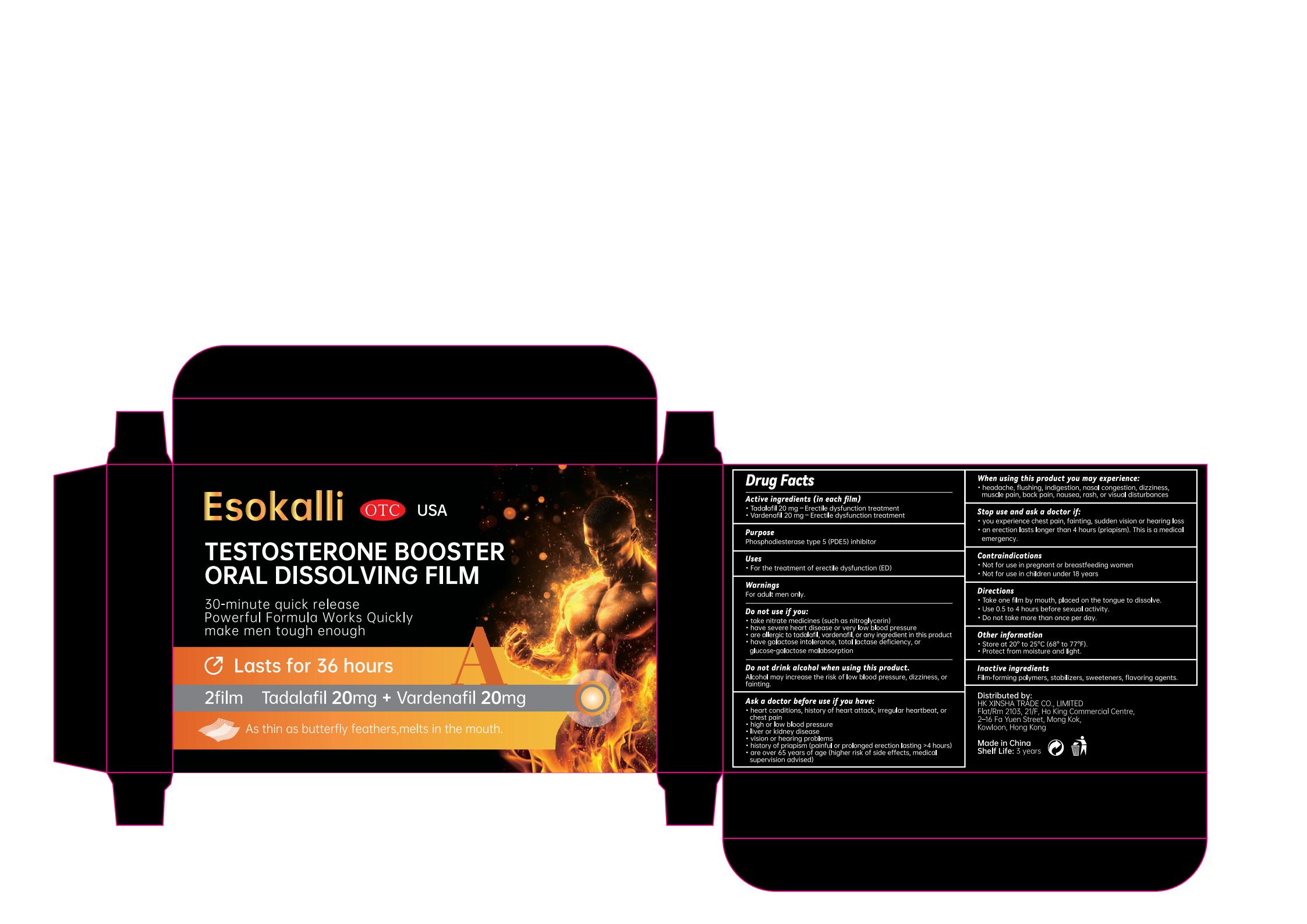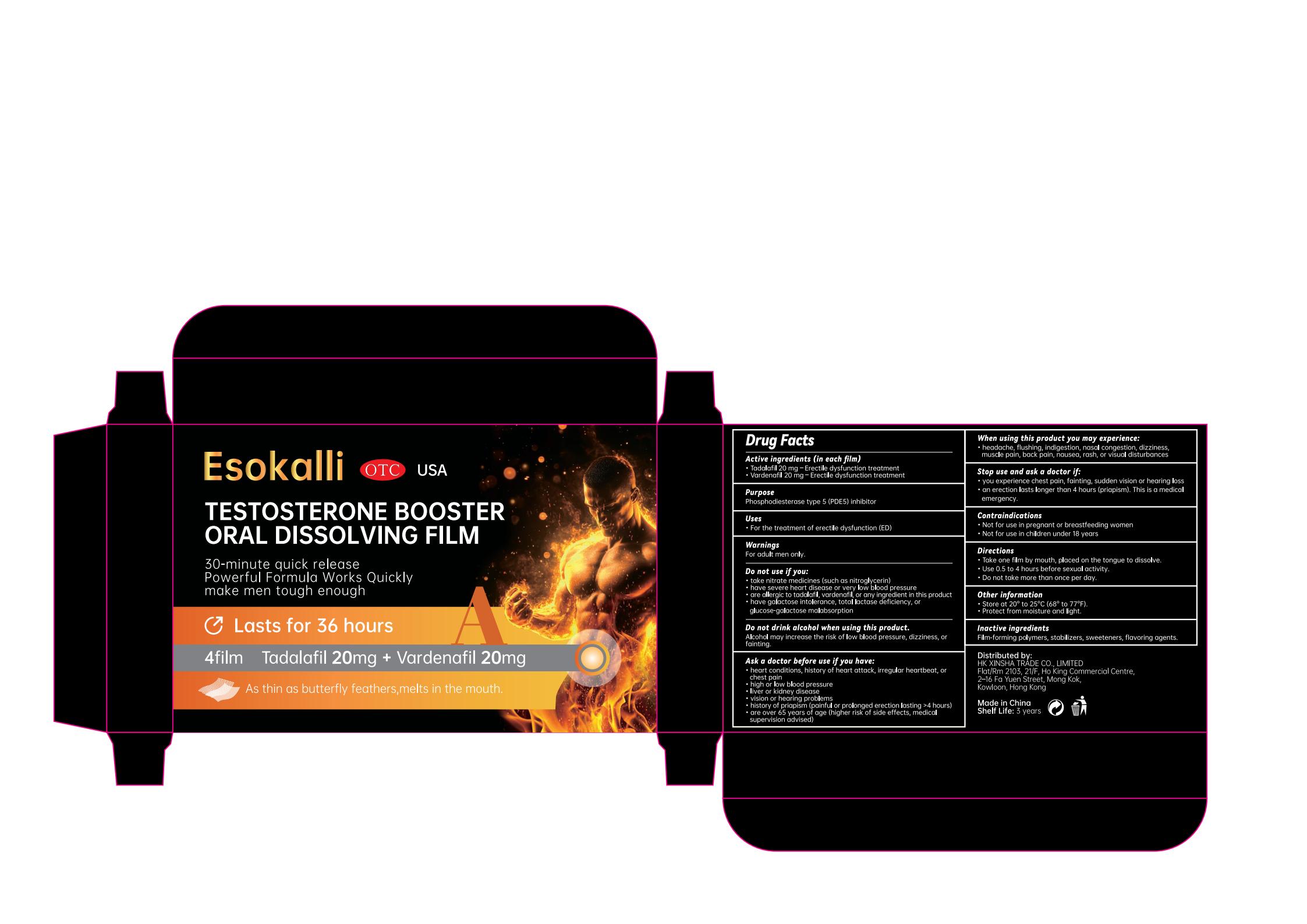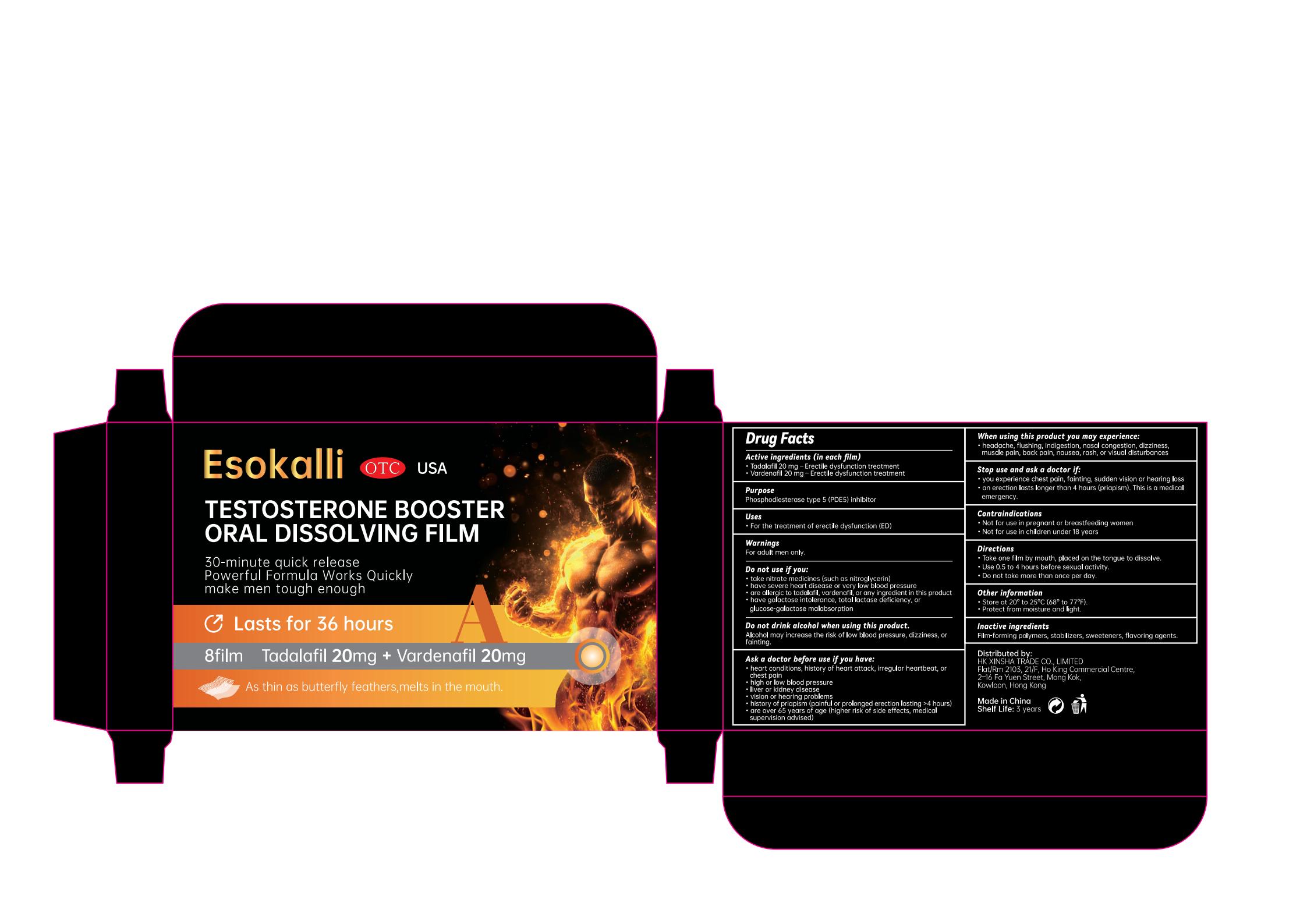 DRUG LABEL: Esokalli Testosterone Booster Oral Dissolving Film
NDC: 84778-079 | Form: LIQUID
Manufacturer: Guangzhou Yixin Cross-border E-commerce Co., Ltd.
Category: otc | Type: HUMAN OTC DRUG LABEL
Date: 20250824

ACTIVE INGREDIENTS: TADALAFIL 20 mg/100 mg; VARDENAFIL 20 mg/100 mg
INACTIVE INGREDIENTS: HYPROMELLOSES; SUCRALOSE; SUCROSE

Active ingredients (in each film)

Tadalafil 20 mg – Erectile dysfunction treatment
Vardenafil 20 mg – Erectile dysfunction treatment

Purpose

Phosphodiesterase type 5 (PDE5) inhibitors

Uses

For the treatment of erectile dysfunction (ED)

Warnings

For prescription use only (Rx only).

Do not use if you are taking any form of nitrate medications (such as nitroglycerin) due to the risk of severe hypotension.
Do not use if allergic to tadalafil, vardenafil, or any component of this product.

Dosage and administration

For external use only.

Do not use

heart problems, history of heart attack, irregular heartbeat, or chest pain
high or low blood pressure
liver or kidney disease
vision or hearing problems
history of priapism (painful or prolonged erection lasting >4 hours)

When using this product you may experience:

headache, flushing, indigestion, nasal congestion, dizziness, muscle pain, back pain, nausea, rash, or visual disturbances

Stop use and ask a doctor if:

you experience chest pain, fainting, sudden vision or hearing loss
an erection lasts longer than 4 hours (priapism). This is a medical emergency.

Contraindications

Pregnant or breastfeeding women
Children under 18 years

Inactive ingredients

Film-forming polymers, stabilizers, sweeteners, flavoring agents.